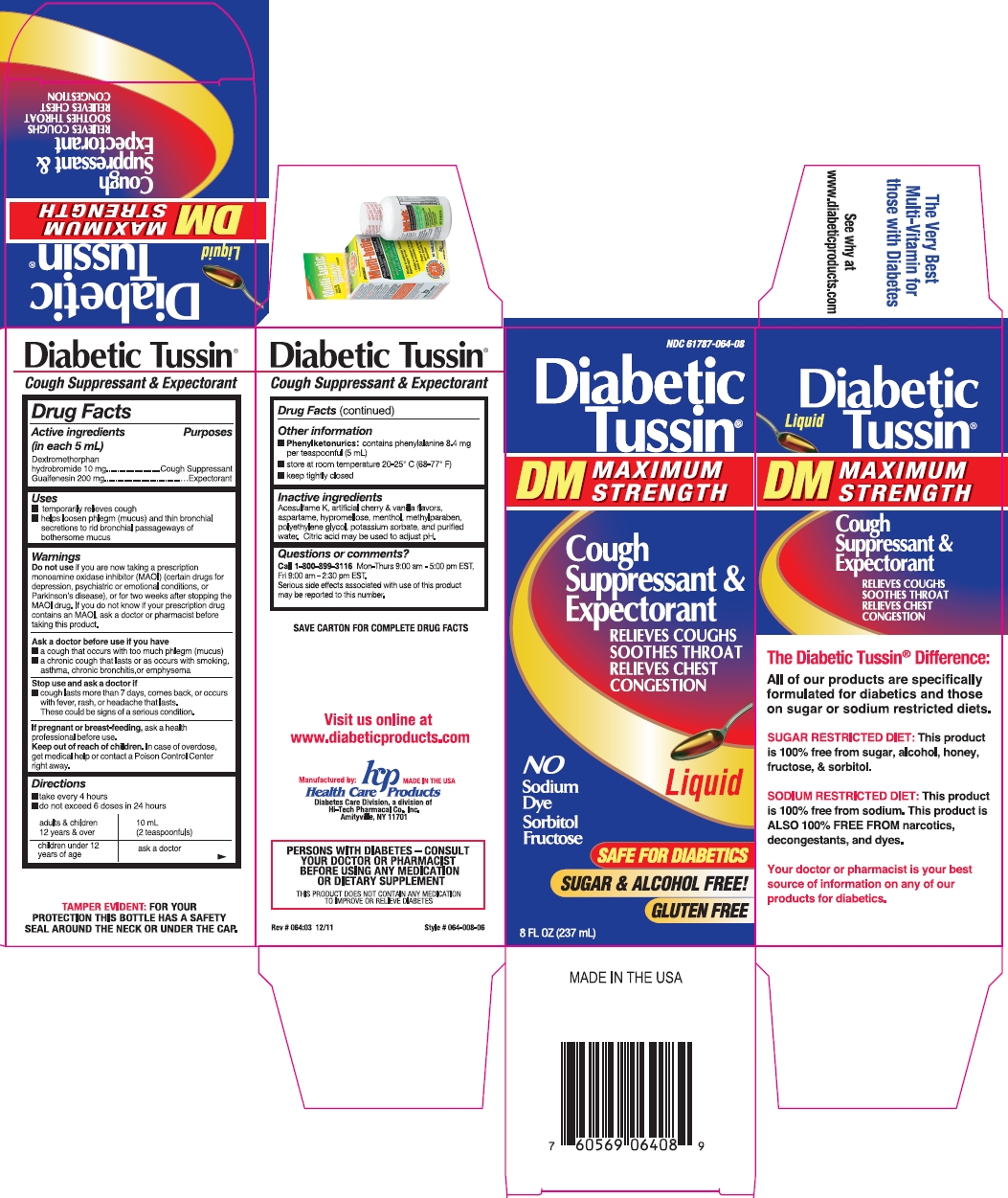 DRUG LABEL: Diabetic Tussin DM Maximum Strength
NDC: 61787-064 | Form: LIQUID
Manufacturer: Health Care Products
Category: otc | Type: HUMAN OTC DRUG LABEL
Date: 20191217

ACTIVE INGREDIENTS: DEXTROMETHORPHAN HYDROBROMIDE 10 mg/5 mL; GUAIFENESIN 200 mg/5 mL
INACTIVE INGREDIENTS: ACESULFAME POTASSIUM; ASPARTAME; HYPROMELLOSE, UNSPECIFIED; MENTHOL, UNSPECIFIED FORM; METHYLPARABEN; POLYETHYLENE GLYCOL, UNSPECIFIED; POTASSIUM SORBATE; WATER; ANHYDROUS CITRIC ACID

Drug Facts

Active ingredients (in each 5 mL)

Dextromethorphan hydrobromide 10 mg

Guaifenesin 200 mg

Purposes

Cough Suppressant

Expectorant

Uses

- temporarily relieves cough
- helps loosen phlegm (mucus) and thin bronchial secretions to rid bronchial passageways of bothersome mucus

Warnings

Do not use

if you are now taking a prescription monoamine oxidase inhibitor (MAOI) (certain drugs for depression, psychiatric or emotional conditions, or Parkinson's disease), or for two weeks after stopping the MAOI drug. If you do not know if your prescription drug contains an MAOI, ask a doctor or pharmacist before taking this product.

Ask a doctor before use if you have

- a cough that occurs with too much phlegm (mucus)
- a chronic cough that lasts or as occurs with smoking, asthma, chronic bronchitis, or emphysema

Stop use and ask a doctor if

- cough lasts more than 7 days, comes back, or occurs with fever, rash, or headache that lasts
These could be signs of a serious condition.

If pregnant or breast-feeding,

ask a health professional before use.

Keep out of reach of children.

In case of overdose, get medical help or contact a Poison Control Center right away.

Directions

- take every 4 hours
- do not exceed 6 doses in 24 hours

adults & children 12 years & over | 10 mL (2 teaspoonfuls)
children under 12 years of age | ask a doctor

Other information

- Phenylketonurics: contains phenylalanine 8.4 mg per teaspoonful (5 mL)
- store at room temperature 20-25ºC (68-77ºF)
- keep tightly closed

Inactive ingredients

Acesulfame K, artificial cherry & vanilla flavors, aspartame, hypromellose, menthol, methylparaben, polyethylene glycol, potassium sorbate, and purified water. Citric acid may be used to adjust pH.

Questions or comments?

Call 1-800-899-3116, Mon-Thurs 9:00 am - 5:00 pm EST, Fri 9:00 am - 2:30 pm EST.

Serious side effects associated with use of this product may be reported to this number.

Rev #064:03 12/11

Package Principal Display Panel

NDC 61787-064-08

Diabetic Tussin®

DM MAXIMUM STRENGTH

Cough Suppressant & Expectorant

RELIEVES COUGHS

SOOTHES THROAT

RELIEVES CHEST CONGESTION

Liquid

No Sodium, Dye, Sorbitol, Fructose

SAFE FOR DIABETICS

SUGAR & ALCOHOL FREE!

GLUTEN FREE

8 FL OZ (237 mL)